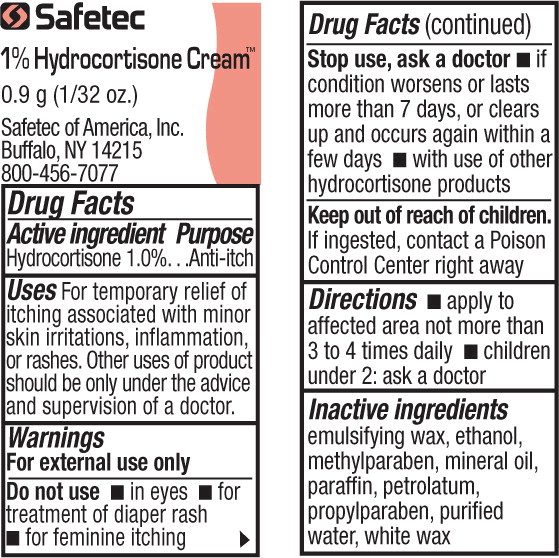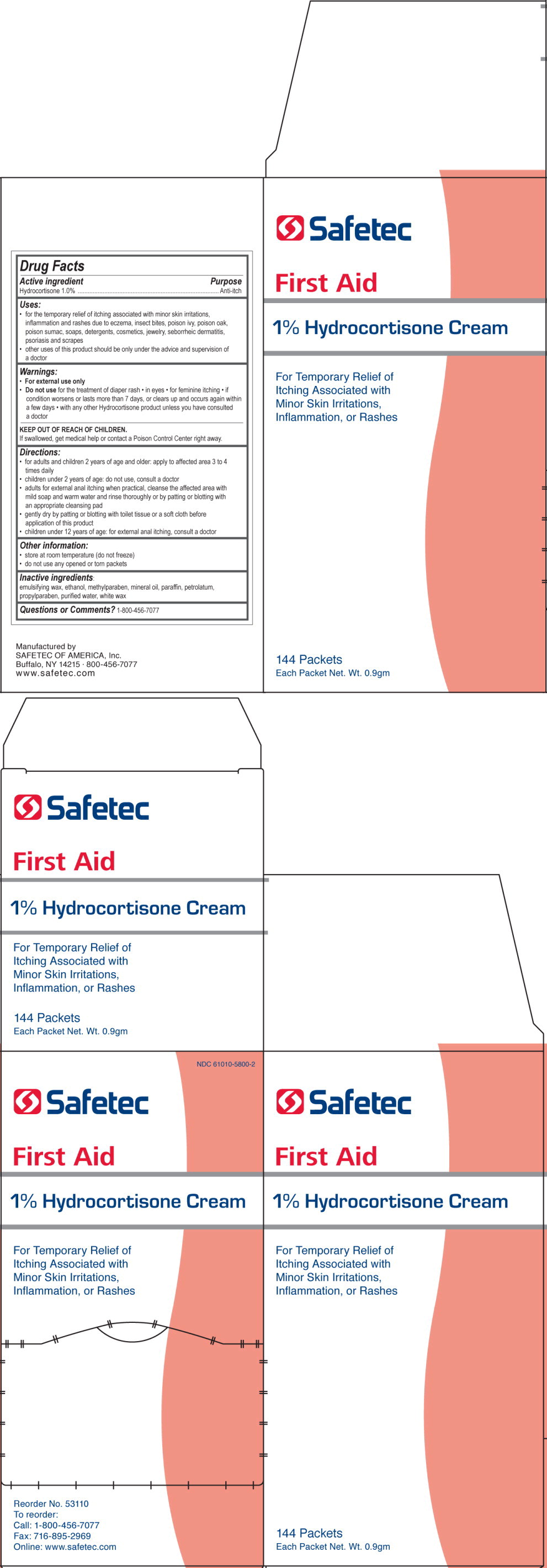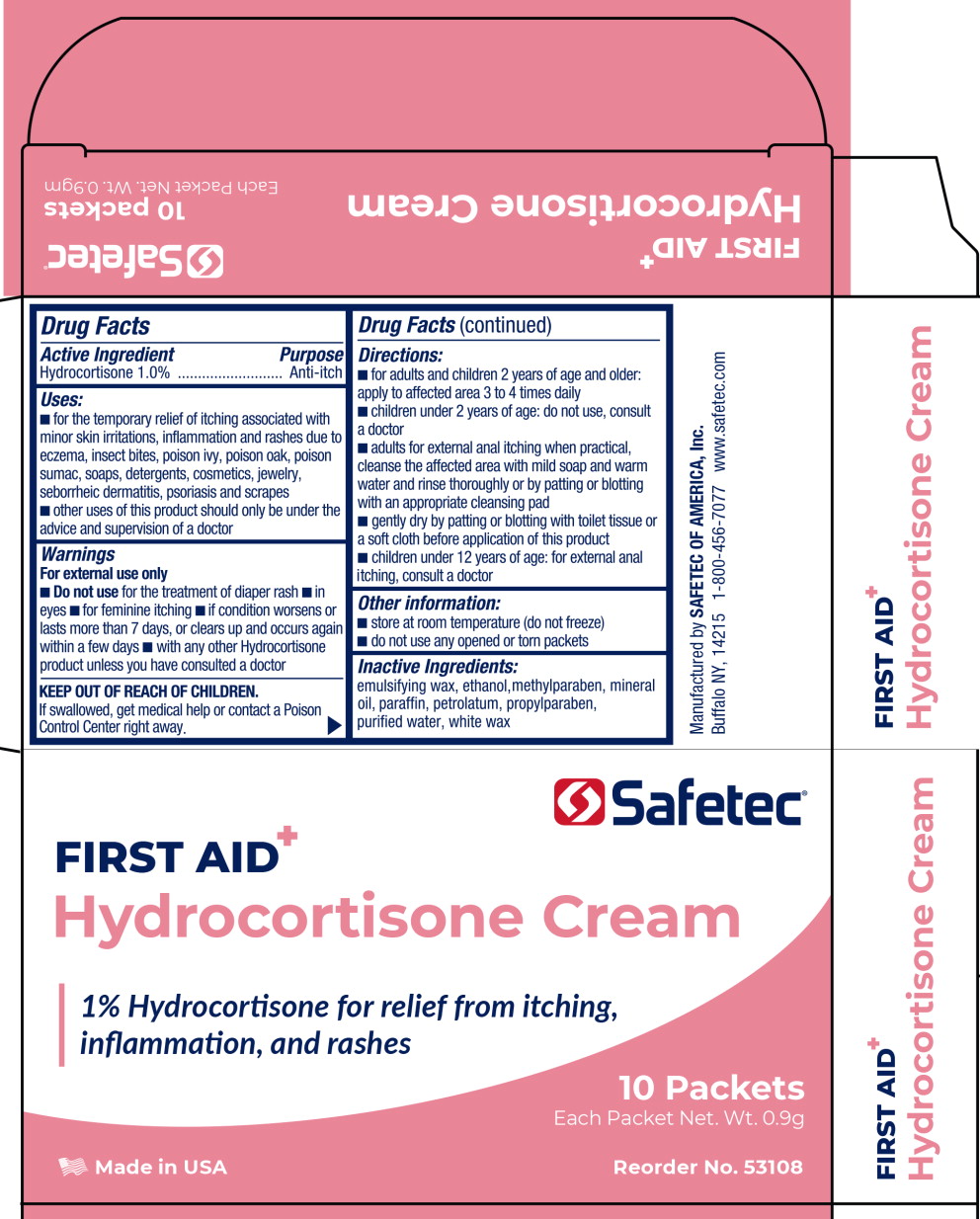 DRUG LABEL: Hydrocortisone
NDC: 61010-5800 | Form: CREAM
Manufacturer: Safetec of America, Inc.
Category: otc | Type: HUMAN OTC DRUG LABEL
Date: 20240207

ACTIVE INGREDIENTS: HYDROCORTISONE 10 mg/1 g
INACTIVE INGREDIENTS: ALCOHOL; METHYLPARABEN; MINERAL OIL; PARAFFIN; PETROLATUM; PROPYLPARABEN; WATER; CETOSTEARYL ALCOHOL; POLYSORBATE 60; PEG-150 DISTEARATE; STEARETH-20

61010-5800,Safetec First Aid 1% Hydrocortisone Cream

Drug Facts

Active ingredient

Hydrocortisone 1.0%

Purpose

Anti-itch

Uses:

- for the temporary relief of itching associated with minor skin irritations, inflammation and rashes due to eczema, insect bites, poison ivy, poison oak, poison sumac, soaps, detergents, cosmetics, jewelry, seborrheic dermatitis, psoriasis and scrapes
- other uses of this product should be only under the advice and supervision of a doctor

Warnings:

- For external use only

- Do not usefor the treatment of diaper rash
- in eyes
- for feminine itching
- if condition worsens or lasts more than 7 days, or clears up and occurs again within a few days
- with any other Hydrocortisone product unless you have consulted a doctor

KEEP OUT OF REACH OF CHILDREN.

If swallowed, get medical help or contact a Poison Control Center right away.

Directions:

- for adults and children 2 years of age and older: apply to affected area 3 to 4 times daily
- children under 2 years of age: do not use, consult a doctor
- adults for external anal itching when practical, cleanse the affected area with mild soap and warm water and rinse thoroughly or by patting or blotting with an appropriate cleansing pad
- gently dry by patting or blotting with toilet tissue or a soft cloth before application of this product
- children under 12 years of age: for external anal itching, consult a doctor

Other information:

- store at room temperature (do not freeze)
- do not use any opened or torn packets

Inactive ingredients:

emulsifying wax, ethanol, methylparaben, mineral oil, paraffin, petrolatum, propylparaben, purified water, white wax

Questions or Comments? 1-800-456-7077

Manufactured by
SAFETEC OF AMERICA, Inc.
Buffalo, NY 14215 . 800-456-7077
www.safetec.com

PRINCIPAL DISPLAY PANEL – 0.9g Pouch Label

Safetec

1% Hydrocortisone Cream™

0.9 g (1/32 oz.)

Safetec of America, Inc.

Buffalo, NY 14215

800-456-7077

PRINCIPAL DISPLAY PANEL – Box Label

NDC 61010-5800-2

Safetec

First Aid

1% Hydrocortisone Cream

For Temporary Relief of

Itching Associated with

Minor Skin Irritations,

Inflammation, or Rashes

Reorder no. 53110

To reorder:

Call: 1-800-456-7077

Fax: 716-895-2969

Online: www.safetec.com

PRINCIPAL DISPLAY PANEL – 10 Packet Box Label

Safetec®

FIRST AID

Hydrocortisone Cream

1% Hydrocortisone for relief from itching,
inflammation, and rashes

10 Packets

Each Packet Net Wt. 0.9g

Made in USA

Reorder no. 53108